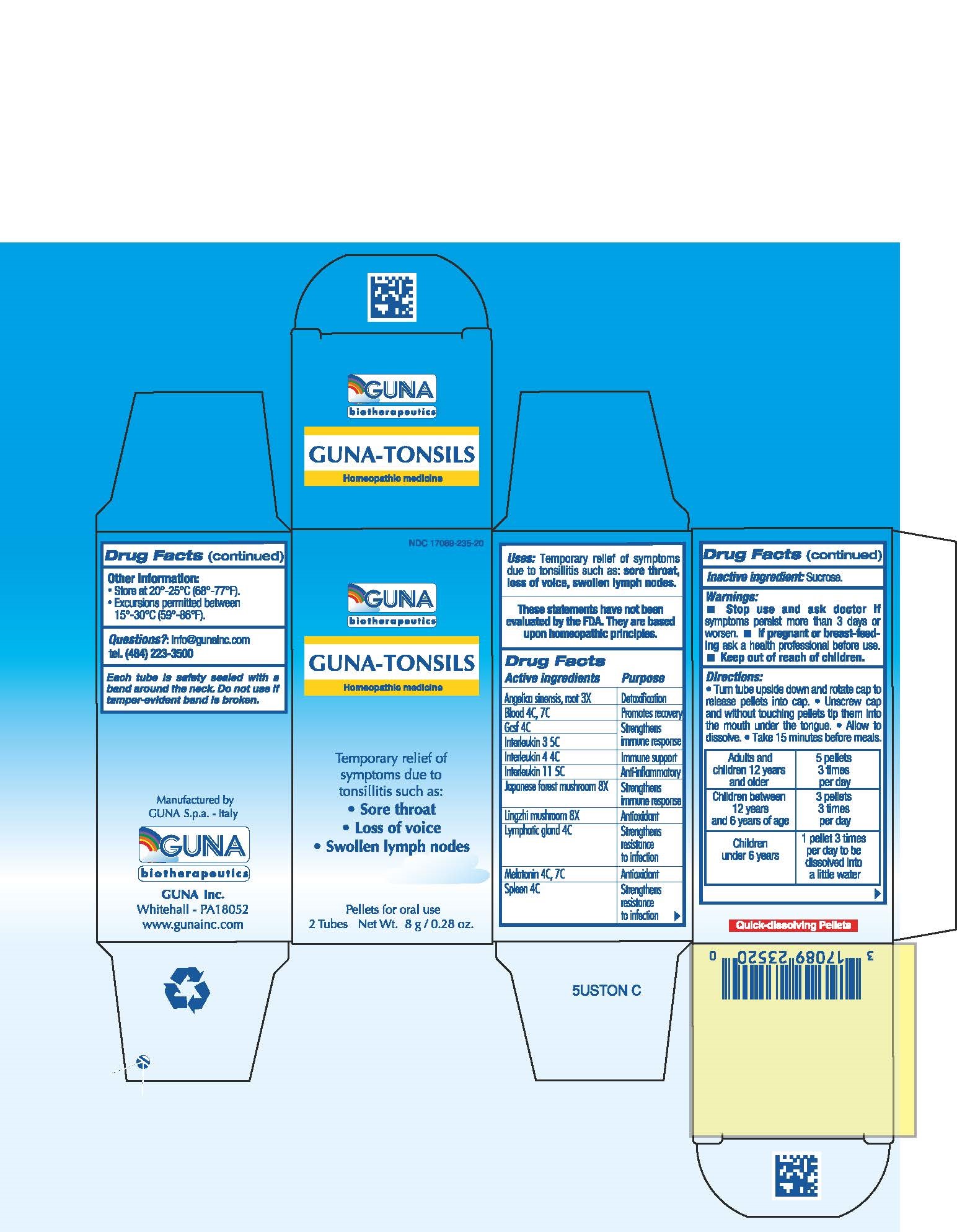 DRUG LABEL: GUNA-TONSILS
NDC: 17089-235 | Form: PELLET
Manufacturer: Guna spa
Category: homeopathic | Type: HUMAN OTC DRUG LABEL
Date: 20181221

ACTIVE INGREDIENTS: ANGELICA SINENSIS ROOT 3 [hp_X]/4 g; SUS SCROFA BLOOD 7 [hp_C]/4 g; LENOGRASTIM 4 [hp_C]/4 g; INTERLEUKIN-11 5 [hp_C]/4 g; INTERLEUKIN-3 5 [hp_C]/4 g; BINETRAKIN 4 [hp_C]/4 g; SHIITAKE MUSHROOM 8 [hp_X]/4 g; REISHI 8 [hp_X]/4 g; SUS SCROFA SMALL INTESTINE MUCOSA LYMPH FOLLICLE 4 [hp_C]/4 g; MELATONIN 4 [hp_C]/4 g; SUS SCROFA SPLEEN 4 [hp_C]/4 g
INACTIVE INGREDIENTS: SUCROSE 3.5 g/4 g

GUNA-TONSILS

ACTIVE INGREDIENTS/PURPOSE

ANGELICA SINENSIS, RADIX 3X DETOXIFICATION
BLOOD 4C, 7C PROMOTES RECOVERY
GCSF 4C STRENGTHENS IMMUNE RESPONSE
INTERLEUKIN 11 5C ANTI-INFLAMMATORY
INTERLEUKIN 3 5C STRENGTHENS IMMUNE RESPONSE
INTERLEUKIN 4 4C IMMUNE SUPPORT
JAPANESE FOREST MUSHROOM 8X STRENGTHENS IMMUNE RESPONSE
LING CHI MUSHROOM 8X ANTIOXIDANT
LYMPHATIC GLAND 4C STRENGTHENS RESISTANCE TO INFECTION
MELATONIN 4C, 7C ANTIOXIDANT
SPLEEN 4C STRENGTHENS RESISTANCE TO INFECTION

USES

Temporary relief of symptoms due to Tonsillitis such as:

- Sore throat
- Loss of voice
- Swollen lymph nodes

WARNINGS

Stop use and ask doctor if symptoms persist more than 5 days or worsen.
If pregnant or breast-feeding ask a health professional before use.
Keep out of reach of children.

PREGNANCY

If pregnant or breast-feeding ask a health professional before use.

WARNINGS

Keep this and all medicines out of reach of children

DIRECTIONS

Take 15 minutes before meals
Adults and children 12 years and older 5 pellets 3 times per day
Children between 12 years and 6 years of age 3 pellets 3 times per day
Children under 6 years 1 pellet 3 times per day to be dissolved into a little water

QUESTIONS

Questions?: info@gunainc.com
tel. (484) 223-3500

INDICATIONS AND USAGE

Turn tube upside down and rotate cap to release pellets into cap.
Unscrew cap and without touching pellets tip them into the mouth under the tongue.
Allow to dissolve
Take 15 minutes before meals.

Inactive ingredient: Sucrose.